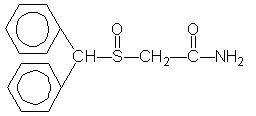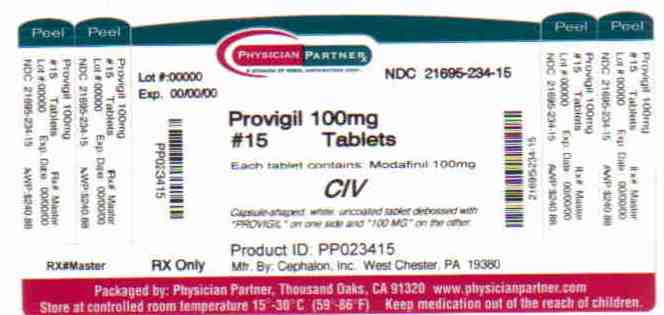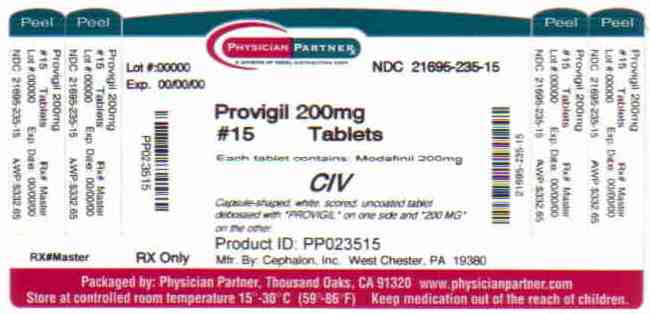 DRUG LABEL: PROVIGIL
NDC: 21695-235 | Form: TABLET
Manufacturer: Rebel Distributors Corp
Category: prescription | Type: HUMAN PRESCRIPTION DRUG LABEL
Date: 20101227
DEA Schedule: CIV

ACTIVE INGREDIENTS: MODAFINIL 200 mg/1 1
INACTIVE INGREDIENTS: CROSCARMELLOSE SODIUM; LACTOSE; MAGNESIUM STEARATE; CELLULOSE, MICROCRYSTALLINE; POVIDONE; STARCH, CORN

PROVIGIL® (modafinil) Tablets [C-IV]

DESCRIPTION

PROVIGIL (modafinil) is a wakefulness-promoting agent for oral administration. Modafinil is a racemic compound. The chemical name for modafinil is 2-[(diphenylmethyl)sulfinyl]acetamide. The molecular formula is C15H15NO2S and the molecular weight is 273.35.

The chemical structure is:

Modafinil is a white to off-white, crystalline powder that is practically insoluble in water and cyclohexane. It is sparingly to slightly soluble in methanol and acetone. PROVIGIL tablets contain 100 mg or 200 mg of modafinil and the following inactive ingredients: lactose, microcrystalline cellulose, pregelatinized starch, croscarmellose sodium, povidone, and magnesium stearate.

CLINICAL PHARMACOLOGY

Mechanism of Action and Pharmacology

The precise mechanism(s) through which modafinil promotes wakefulness is unknown. Modafinil has wake-promoting actions similar to sympathomimetic agents like amphetamine and methylphenidate, although the pharmacologic profile is not identical to that of sympathomimetic amines.

Modafinil has weak to negligible interactions with receptors for norepinephrine, serotonin, dopamine, GABA, adenosine, histamine-3, melatonin, and benzodiazepines. Modafinil also does not inhibit the activities of MAO-B or phosphodiesterases II-V.

Modafinil-induced wakefulness can be attenuated by the α1-adrenergic receptor antagonist prazosin; however, modafinil is inactive in other in vitro assay systems known to be responsive to α-adrenergic agonists, such as the rat vas deferens preparation.

Modafinil is not a direct- or indirect-acting dopamine receptor agonist. However, in vitro, modafinil binds to the dopamine transporter and inhibits dopamine reuptake. This activity has been associated in vivo with increased extracellular dopamine levels in some brain regions of animals. In genetically engineered mice lacking the dopamine transporter (DAT), modafinil lacked wake-promoting activity, suggesting that this activity was DAT-dependent. However, the wake-promoting effects of modafinil, unlike those of amphetamine, were not antagonized by the dopamine receptor antagonist haloperidol in rats. In addition, alpha-methyl-p-tyrosine, a dopamine synthesis inhibitor, blocks the action of amphetamine, but does not block locomotor activity induced by modafinil.

In the cat, equal wakefulness-promoting doses of methylphenidate and amphetamine increased neuronal activation throughout the brain. Modafinil at an equivalent wakefulness-promoting dose selectively and prominently increased neuronal activation in more discrete regions of the brain. The relationship of this finding in cats to the effects of modafinil in humans is unknown.

In addition to its wake-promoting effects and ability to increase locomotor activity in animals, modafinil produces psychoactive and euphoric effects, alterations in mood, perception, thinking, and feelings typical of other CNS stimulants in humans. Modafinil has reinforcing properties, as evidenced by its self-administration in monkeys previously trained to self-administer cocaine. Modafinil was also partially discriminated as stimulant-like.

The optical enantiomers of modafinil have similar pharmacological actions in animals. Two major metabolites of modafinil, modafinil acid and modafinil sulfone, do not appear to contribute to the CNS-activating properties of modafinil.

Pharmacokinetics

Modafinil is a racemic compound, whose enantiomers have different pharmacokinetics (e.g., the half-life of the l-isomer is approximately three times that of the d-isomer in adult humans). The enantiomers do not interconvert. At steady state, total exposure to the l-isomer is approximately three times that for the d-isomer. The trough concentration (Cminss) of circulating modafinil after once daily dosing consists of 90% of the l-isomer and 10% of the d-isomer. The effective elimination half-life of modafinil after multiple doses is about 15 hours. The enantiomers of modafinil exhibit linear kinetics upon multiple dosing of 200-600 mg/day once daily in healthy volunteers. Apparent steady states of total modafinil and l-(-)-modafinil are reached after 2-4 days of dosing.

Absorption

Absorption of PROVIGIL tablets is rapid, with peak plasma concentrations occurring at 2-4 hours. The bioavailability of PROVIGIL tablets is approximately equal to that of an aqueous suspension. The absolute oral bioavailability was not determined due to the aqueous insolubility (<1 mg/mL) of modafinil, which precluded intravenous administration. Food has no effect on overall PROVIGIL bioavailability; however, its absorption (tmax) may be delayed by approximately one hour if taken with food.

Distribution

Modafinil is well distributed in body tissue with an apparent volume of distribution (~0.9 L/kg) larger than the volume of total body water (0.6 L/kg). In human plasma, in vitro, modafinil is moderately bound to plasma protein (~60%, mainly to albumin). At serum concentrations obtained at steady state after doses of 200 mg/day, modafinil exhibits no displacement of protein binding of warfarin, diazepam or propranolol. Even at much larger concentrations (1000µM; > 25 times the Cmax of 40µM at steady state at 400 mg/day), modafinil has no effect on warfarin binding. Modafinil acid at concentrations >500µM decreases the extent of warfarin binding, but these concentrations are >35 times those achieved therapeutically.

Metabolism and Elimination

The major route of elimination is metabolism (~90%), primarily by the liver, with subsequent renal elimination of the metabolites. Urine alkalinization has no effect on the elimination of modafinil.

Metabolism occurs through hydrolytic deamidation, S-oxidation, aromatic ring hydroxylation, and glucuronide conjugation. Less than 10% of an administered dose is excreted as the parent compound. In a clinical study using radiolabeled modafinil, a total of 81% of the administered radioactivity was recovered in 11 days post-dose, predominantly in the urine (80% vs. 1.0% in the feces). The largest fraction of the drug in urine was modafinil acid, but at least six other metabolites were present in lower concentrations. Only two metabolites reach appreciable concentrations in plasma, i.e., modafinil acid and modafinil sulfone. In preclinical models, modafinil acid, modafinil sulfone, 2-[(diphenylmethyl)sulfonyl]acetic acid and 4-hydroxy modafinil, were inactive or did not appear to mediate the arousal effects of modafinil.

In adults, decreases in trough levels of modafinil have sometimes been observed after multiple weeks of dosing, suggesting auto-induction, but the magnitude of the decreases and the inconsistency of their occurrence suggest that their clinical significance is minimal. Significant accumulation of modafinil sulfone has been observed after multiple doses due to its long elimination half-life of 40 hours. Induction of metabolizing enzymes, most importantly cytochrome P-450 (CYP) 3A4, has also been observed in vitro after incubation of primary cultures of human hepatocytes with modafinil and in vivo after extended administration of modafinil at 400 mg/day. (For further discussion of the effects of modafinil on CYP enzyme activities, see PRECAUTIONS, Drug Interactions.)

Drug-Drug Interactions:

Based on in vitro data, modafinil is metabolized partially by the 3A isoform subfamily of hepatic cytochrome P450 (CYP3A4). In addition, modafinil has the potential to inhibit CYP2C19, suppress CYP2C9, and induce CYP3A4, CYP2B6, and CYP1A2. Because modafinil and modafinil sulfone are reversible inhibitors of the drug-metabolizing enzyme CYP2C19, co-administration of modafinil with drugs such as diazepam, phenytoin and propranolol, which are largely eliminated via that pathway, may increase the circulating levels of those compounds. In addition, in individuals deficient in the enzyme CYP2D6 (i.e., 7-10% of the Caucasian population; similar or lower in other populations), the levels of CYP2D6 substrates such as tricyclic antidepressants and selective serotonin reuptake inhibitors, which have ancillary routes of elimination through CYP2C19, may be increased by co-administration of modafinil. Dose adjustments may be necessary for patients being treated with these and similar medications (See PRECAUTIONS, Drug Interactions). An in vitro study demonstrated that armodafinil (one of the enantiomers of modafinil) is a substrate of P-glycoprotein.

Coadministration of modafinil with other CNS active drugs such as methylphenidate and dextroamphetamine did not significantly alter the pharmacokinetics of either drug.

Chronic administration of modafinil 400 mg was found to decrease the systemic exposure to two CYP3A4 substrates, ethinyl estradiol and triazolam, after oral administration suggesting that CYP3A4 had been induced. Chronic administration of modafinil can increase the elimination of substrates of CYP3A4. Dose adjustments may be necessary for patients being treated with these and similar medications (See PRECAUTIONS, Drug Interactions).

An apparent concentration-related suppression of CYP2C9 activity was observed in human hepatocytes after exposure to modafinil in vitro suggesting that there is a potential for a metabolic interaction between modafinil and the substrates of this enzyme (e.g., S-warfarin, phenytoin). However, in an interaction study in healthy volunteers, chronic modafinil treatment did not show a significant effect on the pharmacokinetics of warfarin when compared to placebo. (See PRECAUTIONS, Drug Interactions,Other Drugs, Warfarin).

Special Populations

Gender Effect:

The pharmacokinetics of modafinil are not affected by gender.

Age Effect:

A slight decrease (~20%) in the oral clearance (CL/F) of modafinil was observed in a single dose study at 200 mg in 12 subjects with a mean age of 63 years (range 53 – 72 years), but the change was considered not likely to be clinically significant. In a multiple dose study (300 mg/day) in 12 patients with a mean age of 82 years (range 67 – 87 years), the mean levels of modafinil in plasma were approximately two times those historically obtained in matched younger subjects. Due to potential effects from the multiple concomitant medications with which most of the patients were being treated, the apparent difference in modafinil pharmacokinetics may not be attributable solely to the effects of aging. However, the results suggest that the clearance of modafinil may be reduced in the elderly (See DOSAGE AND ADMINISTRATION).

Race Effect:

The influence of race on the pharmacokinetics of modafinil has not been studied.

Renal Impairment:

In a single dose 200 mg modafinil study, severe chronic renal failure (creatinine clearance ≤ 20 mL/min) did not significantly influence the pharmacokinetics of modafinil, but exposure to modafinil acid (an inactive metabolite) was increased 9-fold (See PRECAUTIONS).

Hepatic Impairment:

Pharmacokinetics and metabolism were examined in patients with cirrhosis of the liver (6 males and 3 females). Three patients had stage B or B+ cirrhosis (per the Child criteria) and 6 patients had stage C or C+ cirrhosis. Clinically 8 of 9 patients were icteric and all had ascites. In these patients, the oral clearance of modafinil was decreased by about 60% and the steady state concentration was doubled compared to normal patients. The dose of PROVIGIL should be reduced in patients with severe hepatic impairment (See PRECAUTIONS and DOSAGE AND ADMINISTRATION).

CLINICAL TRIALS

The effectiveness of PROVIGIL in reducing excessive sleepiness has been established in the following sleep disorders: narcolepsy, obstructive sleep apnea/hypopnea syndrome (OSAHS), and shift work sleep disorder (SWSD).

Narcolepsy

The effectiveness of PROVIGIL in reducing the excessive sleepiness (ES) associated with narcolepsy was established in two US 9-week, multicenter, placebo-controlled, two-dose (200 mg per day and 400 mg per day) parallel-group, double-blind studies of outpatients who met the ICD-9 and American Sleep Disorders Association criteria for narcolepsy (which are also consistent with the American Psychiatric Association DSM-IV criteria). These criteria include either 1) recurrent daytime naps or lapses into sleep that occur almost daily for at least three months, plus sudden bilateral loss of postural muscle tone in association with intense emotion (cataplexy) or 2) a complaint of excessive sleepiness or sudden muscle weakness with associated features: sleep paralysis, hypnagogic hallucinations, automatic behaviors, disrupted major sleep episode; and polysomnography demonstrating one of the following: sleep latency less than 10 minutes or rapid eye movement (REM) sleep latency less than 20 minutes. In addition, for entry into these studies, all patients were required to have objectively documented excessive daytime sleepiness, a Multiple Sleep Latency Test (MSLT) with two or more sleep onset REM periods, and the absence of any other clinically significant active medical or psychiatric disorder. The MSLT, an objective daytime polysomnographic assessment of the patient’s ability to fall asleep in an unstimulating environment, measures latency (in minutes) to sleep onset averaged over 4 test sessions at 2-hour intervals following nocturnal polysomnography. For each test session, the subject was told to lie quietly and attempt to sleep. Each test session was terminated after 20 minutes if no sleep occurred or 15 minutes after sleep onset.

In both studies, the primary measures of effectiveness were 1) sleep latency, as assessed by the Maintenance of Wakefulness Test (MWT) and 2) the change in the patient’s overall disease status, as measured by the Clinical Global Impression of Change (CGI-C). For a successful trial, both measures had to show significant improvement.

The MWT measures latency (in minutes) to sleep onset averaged over 4 test sessions at 2 hour intervals following nocturnal polysomnography. For each test session, the subject was asked to attempt to remain awake without using extraordinary measures. Each test session was terminated after 20 minutes if no sleep occurred or 10 minutes after sleep onset. The CGI-C is a 7-point scale, centered at No Change, and ranging from Very Much Worse to Very Much Improved. Patients were rated by evaluators who had no access to any data about the patients other than a measure of their baseline severity. Evaluators were not given any specific guidance about the criteria they were to apply when rating patients.

Other assessments of effect included the Multiple Sleep Latency Test (MSLT), Epworth Sleepiness Scale (ESS; a series of questions designed to assess the degree of sleepiness in everyday situations) the Steer Clear Performance Test (SCPT; a computer-based evaluation of a patient’s ability to avoid hitting obstacles in a simulated driving situation), standard nocturnal polysomnography, and patient’s daily sleep log. Patients were also assessed with the Quality of Life in Narcolepsy (QOLIN) scale, which contains the validated SF-36 health questionnaire.

Both studies demonstrated improvement in objective and subjective measures of excessive daytime sleepiness for both the 200 mg and 400 mg doses compared to placebo. Patients treated with either dose of PROVIGIL showed a statistically significantly enhanced ability to remain awake on the MWT (all p values <0.001) at weeks 3, 6, 9, and final visit compared to placebo and a statistically significantly greater global improvement, as rated on the CGI-C scale (all p values <0.05).

The average sleep latencies (in minutes) on the MWT at baseline for the 2 controlled trials are shown in Table 1 below, along with the average change from baseline on the MWT at final visit.

The percentages of patients who showed any degree of improvement on the CGI-C in the two clinical trials are shown in Table 2 below.

Similar statistically significant treatment-related improvements were seen on other measures of impairment in narcolepsy, including a patient assessed level of daytime sleepiness on the ESS (p<0.001 for each dose in comparison to placebo).

Nighttime sleep measured with polysomnography was not affected by the use of PROVIGIL.

Obstructive Sleep Apnea/Hypopnea Syndrome (OSAHS)

The effectiveness of PROVIGIL in reducing the excessive sleepiness associated with OSAHS was established in two clinical trials. In both studies, patients were enrolled who met the International Classification of Sleep Disorders (ICSD) criteria for OSAHS (which are also consistent with the American Psychiatric Association DSM-IV criteria). These criteria include either, 1) excessive sleepiness or insomnia, plus frequent episodes of impaired breathing during sleep, and associated features such as loud snoring, morning headaches and dry mouth upon awakening; or 2) excessive sleepiness or insomnia and polysomnography demonstrating one of the following: more than five obstructive apneas, each greater than 10 seconds in duration, per hour of sleep and one or more of the following: frequent arousals from sleep associated with the apneas, bradytachycardia, and arterial oxygen desaturation in association with the apneas. In addition, for entry into these studies, all patients were required to have excessive sleepiness as demonstrated by a score ≥10 on the Epworth Sleepiness Scale, despite treatment with continuous positive airway pressure (CPAP). Evidence that CPAP was effective in reducing episodes of apnea/hypopnea was required along with documentation of CPAP use.

In the first study, a 12-week multicenter placebo-controlled trial, a total of 327 patients were randomized to receive PROVIGIL 200 mg/day, PROVIGIL 400 mg/day, or matching placebo. The majority of patients (80%) were fully compliant with CPAP, defined as CPAP use > 4 hours/night on > 70% nights. The remainder were partially CPAP compliant, defined as CPAP use < 4 hours/night on >30% nights. CPAP use continued throughout the study. The primary measures of effectiveness were 1) sleep latency, as assessed by the Maintenance of Wakefulness Test (MWT) and 2) the change in the patient’s overall disease status, as measured by the Clinical Global Impression of Change (CGI-C) at week 12 or the final visit. (See CLINICAL TRIALS, Narcolepsy section above for a description of these tests.)

Patients treated with PROVIGIL showed a statistically significant improvement in the ability to remain awake compared to placebo-treated patients as measured by the MWT (p<0.001) at endpoint [Table 1]. PROVIGIL-treated patients also showed a statistically significant improvement in clinical condition as rated by the CGI-C scale (p<0.001) [Table 2]. The two doses of PROVIGIL performed similarly.

In the second study, a 4-week multicenter placebo-controlled trial, 157 patients were randomized to either PROVIGIL 400 mg/day or placebo. Documentation of regular CPAP use (at least 4 hours/night on 70% of nights) was required for all patients. The primary outcome measure was the change from baseline on the ESS at week 4 or final visit. The baseline ESS scores for the PROVIGIL and placebo groups were 14.2 and 14.4, respectively. At week 4, the ESS was reduced by 4.6 in the PROVIGIL group and by 2.0 in the placebo group, a difference that was statistically significant (p<0.0001).

Nighttime sleep measured with polysomnography was not affected by the use of PROVIGIL.

Shift Work Sleep Disorder (SWSD)

The effectiveness of PROVIGIL for the excessive sleepiness associated with SWSD was demonstrated in a 12-week placebo-controlled clinical trial. A total of 209 patients with chronic SWSD were randomized to receive PROVIGIL 200 mg/day or placebo. All patients met the International Classification of Sleep Disorders (ICSD-10) criteria for chronic SWSD (which are consistent with the American Psychiatric Association DSM-IV criteria for Circadian Rhythm Sleep Disorder: Shift Work Type). These criteria include 1) either: a) a primary complaint of excessive sleepiness or insomnia which is temporally associated with a work period (usually night work) that occurs during the habitual sleep phase, or b) polysomnography and the MSLT demonstrate loss of a normal sleep-wake pattern (i.e., disturbed chronobiological rhythmicity); and 2) no other medical or mental disorder accounts for the symptoms, and 3) the symptoms do not meet criteria for any other sleep disorder producing insomnia or excessive sleepiness (e.g., time zone change [jet lag] syndrome).

It should be noted that not all patients with a complaint of sleepiness who are also engaged in shift work meet the criteria for the diagnosis of SWSD. In the clinical trial, only patients who were symptomatic for at least 3 months were enrolled.

Enrolled patients were also required to work a minimum of 5 night shifts per month, have excessive sleepiness at the time of their night shifts (MSLT score < 6 minutes), and have daytime insomnia documented by a daytime polysomnogram (PSG).

The primary measures of effectiveness were 1) sleep latency, as assessed by the Multiple Sleep Latency Test (MSLT) performed during a simulated night shift at week 12 or the final visit and 2) the change in the patient’s overall disease status, as measured by the Clinical Global Impression of Change (CGI-C) at week 12 or the final visit. Patients treated with PROVIGIL showed a statistically significant prolongation in the time to sleep onset compared to placebo-treated patients, as measured by the nighttime MSLT [Table 1] (p<0.05). Improvement on the CGI-C was also observed to be statistically significant (p<0.001). (See CLINICAL TRIALS, Narcolepsy section above for a description of these tests.)

Daytime sleep measured with polysomnography was not affected by the use of PROVIGIL.

Table 1. Average Baseline Sleep Latency and Change from Baseline at Final Visit in Adults (MWT and MSLT in minutes)
Disorder | Measure | PROVIGIL 200 mg* |  | PROVIGIL 400 mg* |  | Placebo
 |  | Baseline | Change from Baseline | Baseline | Change from Baseline | Baseline | Change from Baseline
Narcolepsy I | MWT | 5.8 | 2.3 | 6.6 | 2.3 | 5.8 | -0.7
Narcolepsy II | MWT | 6.1 | 2.2 | 5.9 | 2.0 | 6.0 | -0.7
OSAHS | MWT | 13.1 | 1.6 | 13.6 | 1.5 | 13.8 | -1.1
SWSD | MSLT | 2.1 | 1.7 | - | - | 2.0 | 0.3
*Significantly different than placebo for all trials (p<0.01 for all trials but SWSD, which was p<0.05)

Table 2. Clinical Global Impression of Change (CGI-C) (Percent of Adult Patients Who Improved at Final Visit)
Disorder | PROVIGIL 200 mg* | PROVIGIL 400 mg* | Placebo
Narcolepsy I | 64% | 72% | 37%
Narcolepsy II | 58% | 60% | 38%
OSAHS | 61% | 68% | 37%
SWSD | 74% | - | 36%
*Significantly different than placebo for all trials (p<0.01)

INDICATIONS AND USAGE

PROVIGIL is indicated to improve wakefulness in adult patients with excessive sleepiness associated with narcolepsy, obstructive sleep apnea/hypopnea syndrome, and shift work sleep disorder.

In OSAHS, PROVIGIL is indicated as an adjunct to standard treatment(s) for the underlying obstruction. If continuous positive airway pressure (CPAP) is the treatment of choice for a patient, a maximal effort to treat with CPAP for an adequate period of time should be made prior to initiating PROVIGIL. If PROVIGIL is used adjunctively with CPAP, the encouragement of and periodic assessment of CPAP compliance is necessary.

In all cases, careful attention to the diagnosis and treatment of the underlying sleep disorder(s) is of utmost importance. Prescribers should be aware that some patients may have more than one sleep disorder contributing to their excessive sleepiness.

The effectiveness of modafinil in long-term use (greater than 9 weeks in Narcolepsy clinical trials and 12 weeks in OSAHS and SWSD clinical trials) has not been systematically evaluated in placebo-controlled trials. The physician who elects to prescribe PROVIGIL for an extended time in patients with Narcolepsy, OSAHS, or SWSD should periodically reevaluate long-term usefulness for the individual patient.

CONTRAINDICATIONS

PROVIGIL is contraindicated in patients with known hypersensitivity to modafinil, armodafinil or its inactive ingredients.

WARNINGS

Serious Rash, including Stevens-Johnson Syndrome

Serious rash requiring hospitalization and discontinuation of treatment has been reported in adults and children in association with the use of modafinil.

Modafinil is not approved for use in pediatric patients for any indication.

In clinical trials of modafinil, the incidence of rash resulting in discontinuation was approximately 0.8% (13 per 1,585) in pediatric patients (age <17 years); these rashes included 1 case of possible Stevens-Johnson Syndrome (SJS) and 1 case of apparent multi-organ hypersensitivity reaction. Several of the cases were associated with fever and other abnormalities (e.g., vomiting, leukopenia). The median time to rash that resulted in discontinuation was 13 days. No such cases were observed among 380 pediatric patients who received placebo. No serious skin rashes have been reported in adult clinical trials (0 per 4,264) of modafinil.

Rare cases of serious or life-threatening rash, including SJS, Toxic Epidermal Necrolysis (TEN), and Drug Rash with Eosinophilia and Systemic Symptoms (DRESS) have been reported in adults and children in worldwide post-marketing experience. The reporting rate of TEN and SJS associated with modafinil use, which is generally accepted to be an underestimate due to underreporting, exceeds the background incidence rate. Estimates of the background incidence rate for these serious skin reactions in the general population range between 1 to 2 cases per million-person years.

There are no factors that are known to predict the risk of occurrence or the severity of rash associated with modafinil. Nearly all cases of serious rash associated with modafinil occurred within 1 to 5 weeks after treatment initiation. However, isolated cases have been reported after prolonged treatment (e.g., 3 months). Accordingly, duration of therapy cannot be relied upon as a means to predict the potential risk heralded by the first appearance of a rash.

Although benign rashes also occur with modafinil, it is not possible to reliably predict which rashes will prove to be serious. Accordingly, modafinil should ordinarily be discontinued at the first sign of rash, unless the rash is clearly not drug-related. Discontinuation of treatment may not prevent a rash from becoming life-threatening or permanently disabling or disfiguring.

Angioedema and Anaphylactoid Reactions

One serious case of angioedema and one case of hypersensitivity (with rash, dysphagia, and bronchospasm), were observed among 1,595 patients treated with armodafinil, the R enantiomer of modafinil (which is the racemic mixture). No such cases were observed in modafinil clinical trials. However, angioedema has been reported in postmarketing experience with modafinil. Patients should be advised to discontinue therapy and immediately report to their physician any signs or symptoms suggesting angioedema or anaphylaxis (e.g., swelling of face, eyes, lips, tongue or larynx; difficulty in swallowing or breathing; hoarseness).

Multi-organ hypersensitivity reactions, including at least one fatality in postmarketing experience, have occurred in close temporal association (median time to detection 13 days: range 4-33) to the initiation of modafinil.

Although there have been a limited number of reports, multi-organ hypersensitivity reactions may result in hospitalization or be life-threatening. There are no factors that are known to predict the risk of occurrence or the severity of multi-organ hypersensitivity reactions associated with modafinil. Signs and symptoms of this disorder were diverse; however, patients typically, although not exclusively, presented with fever and rash associated with other organ system involvement. Other associated manifestations included myocarditis, hepatitis, liver function test abnormalities, hematological abnormalities (e.g., eosinophilia, leukopenia, thrombocytopenia), pruritus, and asthenia. Because multi-organ hypersensitivity is variable in its expression, other organ system symptoms and signs, not noted here, may occur.

If a multi-organ hypersensitivity reaction is suspected, PROVIGIL should be discontinued. Although there are no case reports to indicate cross-sensitivity with other drugs that produce this syndrome, the experience with drugs associated with multi-organ hypersensitivity would indicate this to be a possibility.

Persistent Sleepiness

Patients with abnormal levels of sleepiness who take PROVIGIL should be advised that their level of wakefulness may not return to normal. Patients with excessive sleepiness, including those taking PROVIGIL, should be frequently reassessed for their degree of sleepiness and, if appropriate, advised to avoid driving or any other potentially dangerous activity. Prescribers should also be aware that patients may not acknowledge sleepiness or drowsiness until directly questioned about drowsiness or sleepiness during specific activities.

Psychiatric Symptoms

Psychiatric adverse experiences have been reported in patients treated with modafinil. Postmarketing adverse events associated with the use of modafinil have included mania, delusions, hallucinations, suicidal ideation and aggression, some resulting in hospitalization. Many, but not all, patients had a prior psychiatric history. One healthy male volunteer developed ideas of reference, paranoid delusions, and auditory hallucinations in association with multiple daily 600 mg doses of modafinil and sleep deprivation. There was no evidence of psychosis 36 hours after drug discontinuation.

In the adult modafinil controlled trials database, psychiatric symptoms resulting in treatment discontinuation (at a frequency >0.3%) and reported more often in patients treated with modafinil compared to those treated with placebo were anxiety (1%), nervousness (1%), insomnia (<1%), confusion (<1%), agitation (<1%), and depression (<1%). Caution should be exercised when PROVIGIL is given to patients with a history of psychosis, depression, or mania. Consideration should be given to the possible emergence or exacerbation of psychiatric symptoms in patients treated with PROVIGIL. If psychiatric symptoms develop in association with PROVIGIL administration, consider discontinuing PROVIGIL.

PRECAUTIONS

Diagnosis of Sleep Disorders

PROVIGIL should be used only in patients who have had a complete evaluation of their excessive sleepiness, and in whom a diagnosis of either narcolepsy, OSAHS, and/or SWSD has been made in accordance with ICSD or DSM diagnostic criteria (See CLINICAL TRIALS). Such an evaluation usually consists of a complete history and physical examination, and it may be supplemented with testing in a laboratory setting. Some patients may have more than one sleep disorder contributing to their excessive sleepiness (e.g., OSAHS and SWSD coincident in the same patient).

General

Although modafinil has not been shown to produce functional impairment, any drug affecting the CNS may alter judgment, thinking or motor skills. Patients should be cautioned about operating an automobile or other hazardous machinery until they are reasonably certain that PROVIGIL therapy will not adversely affect their ability to engage in such activities.

CPAP Use in Patients with OSAHS

In OSAHS, PROVIGIL is indicated as an adjunct to standard treatment(s) for the underlying obstruction. If continuous positive airway pressure (CPAP) is the treatment of choice for a patient, a maximal effort to treat with CPAP for an adequate period of time should be made prior to initiating PROVIGIL. If PROVIGIL is used adjunctively with CPAP, the encouragement of and periodic assessment of CPAP compliance is necessary.

Cardiovascular System

Modafinil has not been evaluated in patients with a recent history of myocardial infarction or unstable angina, and such patients should be treated with caution.

In clinical studies of PROVIGIL, signs and symptoms including chest pain, palpitations, dyspnea and transient ischemic T-wave changes on ECG were observed in three subjects in association with mitral valve prolapse or left ventricular hypertrophy. It is recommended that PROVIGIL tablets not be used in patients with a history of left ventricular hypertrophy or in patients with mitral valve prolapse who have experienced the mitral valve prolapse syndrome when previously receiving CNS stimulants. Such signs may include but are not limited to ischemic ECG changes, chest pain, or arrhythmia. If new onset of any of these symptoms occurs, consider cardiac evaluation.

Blood pressure monitoring in short-term (<3 months) controlled trials showed no clinically significant changes in mean systolic and diastolic blood pressure in patients receiving PROVIGIL as compared to placebo. However, a retrospective analysis of the use of antihypertensive medication in these studies showed that a greater proportion of patients on PROVIGIL required new or increased use of antihypertensive medications (2.4%) compared to patients on placebo (0.7%). The differential use was slightly larger when only studies in OSAHS were included, with 3.4% of patients on PROVIGIL and 1.1% of patients on placebo requiring such alterations in the use of antihypertensive medication. Increased monitoring of blood pressure may be appropriate in patients on PROVIGIL.

Patients Using Steroidal Contraceptives

The effectiveness of steroidal contraceptives may be reduced when used with PROVIGIL tablets and for one month after discontinuation of therapy (See PRECAUTIONS, Drug Interactions). Alternative or concomitant methods of contraception are recommended for patients treated with PROVIGIL tablets, and for one month after discontinuation of PROVIGIL.

Patients Using Cyclosporine

The blood levels of cyclosporine may be reduced when used with PROVIGIL (See PRECAUTIONS, Drug Interactions). Monitoring of circulating cyclosporine concentrations and appropriate dosage adjustment for cyclosporine should be considered when these drugs are used concomitantly.

Patients with Severe Hepatic Impairment

In patients with severe hepatic impairment, with or without cirrhosis (See CLINICAL PHARMACOLOGY), PROVIGIL should be administered at a reduced dose (See DOSAGE AND ADMINISTRATION).

Patients with Severe Renal Impairment

There is inadequate information to determine safety and efficacy of dosing in patients with severe renal impairment. (For pharmacokinetics in renal impairment, see CLINICAL PHARMACOLOGY.)

Elderly Patients

In elderly patients, elimination of modafinil and its metabolites may be reduced as a consequence of aging. Therefore, consideration should be given to the use of lower doses in this population. (See CLINICAL PHARMACOLOGY and DOSAGE AND ADMINISTRATION).

Information for Patients

Physicians are advised to discuss the following issues with patients for whom they prescribe PROVIGIL.

PROVIGIL is indicated for patients who have abnormal levels of sleepiness. PROVIGIL has been shown to improve, but not eliminate this abnormal tendency to fall asleep. Therefore, patients should not alter their previous behavior with regard to potentially dangerous activities (e.g., driving, operating machinery) or other activities requiring appropriate levels of wakefulness, until and unless treatment with PROVIGIL has been shown to produce levels of wakefulness that permit such activities. Patients should be advised that PROVIGIL is not a replacement for sleep.

Patients should be informed that it may be critical that they continue to take their previously prescribed treatments (e.g., patients with OSAHS receiving CPAP should continue to do so).

Patients should be informed of the availability of a patient information leaflet, and they should be instructed to read the leaflet prior to taking PROVIGIL. See Patient Information at the end of this labeling for the text of the leaflet provided for patients.

Patients should be advised to contact their physician if they experience chest pain, rash, depression, anxiety, or signs of psychosis or mania.

Pregnancy

Patients should be advised to notify their physician if they become pregnant or intend to become pregnant during therapy. Patients should be cautioned regarding the potential increased risk of pregnancy when using steroidal contraceptives (including depot or implantable contraceptives) with PROVIGIL and for one month after discontinuation of therapy (See Carcinogenesis, Mutagenesis, Impairment of Fertility and Pregnancy).

Nursing

Patients should be advised to notify their physician if they are breastfeeding an infant.

Concomitant Medication

Patients should be advised to inform their physician if they are taking, or plan to take, any prescription or over-the-counter drugs, because of the potential for interactions between PROVIGIL and other drugs.

Alcohol

Patients should be advised that the use of PROVIGIL in combination with alcohol has not been studied. Patients should be advised that it is prudent to avoid alcohol while taking PROVIGIL.

Allergic Reactions

Patients should be advised to stop taking PROVIGIL and to notify their physician if they develop a rash, hives, mouth sores, blisters, peeling skin, trouble swallowing or breathing or a related allergic phenomenon.

Drug Interactions

CNS Active Drugs

Methylphenidate

In a single-dose study in healthy volunteers, simultaneous administration of modafinil (200 mg) with methylphenidate (40 mg) did not cause any significant alterations in the pharmacokinetics of either drug. However, the absorption of PROVIGIL may be delayed by approximately one hour when coadministered with methylphenidate.

In a multiple-dose, steady-state study in healthy volunteers, modafinil was administered once daily at 200 mg/day for 7 days followed by 400 mg/day for 21 days. Administration of methylphenidate (20 mg/day) during days 22-28 of modafinil treatment 8 hours after the daily dose of modafinil did not cause any significant alterations in the pharmacokinetics of modafinil.

Dextroamphetamine

In a single dose study in healthy volunteers, simultaneous administration of modafinil (200 mg) with dextroamphetamine (10 mg) did not cause any significant alterations in the pharmacokinetics of either drug. However, the absorption of PROVIGIL may be delayed by approximately one hour when coadministered with dextroamphetamine.

In a multiple-dose, steady-state study in healthy volunteers, modafinil was administered once daily at 200 mg/day for 7 days followed by 400 mg/day for 21 days. Administration of dextroamphetamine (20 mg/day) during days 22-28 of modafinil treatment 7 hours after the daily dose of modafinil did not cause any significant alterations in the pharmacokinetics of modafinil.

Clomipramine

The coadministration of a single dose of clomipramine (50 mg) on the first of three days of treatment with modafinil (200 mg/day) in healthy volunteers did not show an effect on the pharmacokinetics of either drug. However, one incident of increased levels of clomipramine and its active metabolite desmethylclomipramine has been reported in a patient with narcolepsy during treatment with modafinil.

Triazolam

In the drug interaction study between PROVIGIL and ethinyl estradiol (EE2), on the same days as those for the plasma sampling for EE2 pharmacokinetics, a single dose of triazolam (0.125 mg) was also administered. Mean Cmax and AUC0-∞ of triazolam were decreased by 42% and 59%, respectively, and its elimination half-life was decreased by approximately an hour after the modafinil treatment.

Monoamine Oxidase (MAO) Inhibitors

Interaction studies with monoamine oxidase inhibitors have not been performed. Therefore, caution should be used when concomitantly administering MAO inhibitors and modafinil.

Other Drugs

Warfarin

There were no significant changes in the pharmacokinetic profiles of R- and S-warfarin in healthy subjects given a single dose of racemic warfarin (5 mg) following chronic administration of modafinil (200 mg/day for 7 days followed by 400 mg/day for 27 days) relative to the profiles in subjects given placebo. However, more frequent monitoring of prothrombin times/INR is advisable whenever PROVIGIL is coadministered with warfarin (See CLINICAL PHARMACOLOGY, Pharmacokinetics, Drug-Drug Interactions)

Ethinyl Estradiol

Administration of modafinil to female volunteers once daily at 200 mg/day for 7 days followed by 400 mg/day for 21 days resulted in a mean 11% decrease in Cmax and 18% decrease in AUC0-24 of ethinyl estradiol (EE2; 0.035 mg; administered orally with norgestimate). There was no apparent change in the elimination rate of ethinyl estradiol.

Cyclosporine

One case of an interaction between modafinil and cyclosporine, a substrate of CYP3A4, has been reported in a 41 year old woman who had undergone an organ transplant. After one month of administration of 200 mg/day of modafinil, cyclosporine blood levels were decreased by 50%. The interaction was postulated to be due to the increased metabolism of cyclosporine, since no other factor expected to affect the disposition of the drug had changed. Dosage adjustment for cyclosporine may be needed.

Potential Interactions with Drugs That Inhibit, Induce, or are Metabolized by Cytochrome P-450 Isoenzymes and Other Hepatic Enzymes

In in vitro studies using primary human hepatocyte cultures, modafinil was shown to slightly induce CYP1A2, CYP2B6 and CYP3A4 in a concentration-dependent manner. Although induction results based on in vitro experiments are not necessarily predictive of response in vivo, caution needs to be exercised when PROVIGIL is coadministered with drugs that depend on these three enzymes for their clearance. Specifically, lower blood levels of such drugs could result (See Other Drugs, Cyclosporine above).

The exposure of human hepatocytes to modafinil in vitro produced an apparent concentration-related suppression of expression of CYP2C9 activity suggesting that there is a potential for a metabolic interaction between modafinil and the substrates of this enzyme (e.g., S-warfarin and phenytoin). In a subsequent clinical study in healthy volunteers, chronic modafinil treatment did not show a significant effect on the single-dose pharmacokinetics of warfarin when compared to placebo (see PRECAUTIONS, Drug Interactions, Warfarin).

In vitro studies using human liver microsomes showed that modafinil reversibly inhibited CYP2C19 at pharmacologically relevant concentrations of modafinil. CYP2C19 is also reversibly inhibited, with similar potency, by a circulating metabolite, modafinil sulfone. Although the maximum plasma concentrations of modafinil sulfone are much lower than those of parent modafinil, the combined effect of both compounds could produce sustained partial inhibition of the enzyme. Drugs that are largely eliminated via CYP2C19 metabolism, such as diazepam, propranolol, phenytoin (also via CYP2C9) or S-mephenytoin may have prolonged elimination upon coadministration with PROVIGIL and may require dosage reduction and monitoring for toxicity.

Tricyclic antidepressants

CYP2C19 also provides an ancillary pathway for the metabolism of certain tricyclic antidepressants (e.g., clomipramine and desipramine) that are primarily metabolized by CYP2D6. In tricyclic-treated patients deficient in CYP2D6 (i.e., those who are poor metabolizers of debrisoquine; 7-10% of the Caucasian population; similar or lower in other populations), the amount of metabolism by CYP2C19 may be substantially increased. PROVIGIL may cause elevation of the levels of the tricyclics in this subset of patients. Physicians should be aware that a reduction in the dose of tricyclic agents might be needed in these patients.

In addition, due to the partial involvement of CYP3A4 in the metabolic elimination of modafinil, coadministration of potent inducers of CYP3A4 (e.g., carbamazepine, phenobarbital, rifampin) or inhibitors of CYP3A4 (e.g., ketoconazole, itraconazole) could alter the plasma levels of modafinil.

Carcinogenesis, Mutagenesis, Impairment of Fertility

Carcinogenesis

Carcinogenicity studies were conducted in which modafinil was administered in the diet to mice for 78 weeks and to rats for 104 weeks at doses of 6, 30, and 60 mg/kg/day. The highest dose studied is 1.5 (mouse) or 3 (rat) times greater than the recommended adult human daily dose of modafinil (200 mg) on a mg/m^2 basis. There was no evidence of tumorigenesis associated with modafinil administration in these studies. However, since the mouse study used an inadequate high dose that was not representative of a maximum tolerated dose, a subsequent carcinogenicity study was conducted in the Tg.AC transgenic mouse. Doses evaluated in the Tg.AC assay were 125, 250, and 500 mg/kg/day, administered dermally. There was no evidence of tumorigenicity associated with modafinil administration; however, this dermal model may not adequately assess the carcinogenic potential of an orally administered drug.

Mutagenesis

Modafinil demonstrated no evidence of mutagenic or clastogenic potential in a series of in vitro (i.e., bacterial reverse mutation assay, mouse lymphoma tk assay, chromosomal aberration assay in human lymphocytes, cell transformation assay in BALB/3T3 mouse embryo cells) assays in the absence or presence of metabolic activation, or in vivo (mouse bone marrow micronucleus) assays. Modafinil was also negative in the unscheduled DNA synthesis assay in rat hepatocytes.

Impairment of Fertility

Oral administration of modafinil (doses of up to 480 mg/kg/day) to male and female rats prior to and throughout mating, and continuing in females through day 7 of gestation produced an increase in the time to mate at the highest dose; no effects were observed on other fertility or reproductive parameters. The no-effect dose of 240 mg/kg/day was associated with a plasma modafinil exposure (AUC) approximately equal to that in humans at the recommended dose of 200 mg.

Pregnancy

Pregnancy Category C:

In studies conducted in rats and rabbits, developmental toxicity was observed at clinically relevant exposures.

Modafinil (50, 100, or 200 mg/kg/day) administered orally to pregnant rats throughout the period of organogenesis caused, in the absence of maternal toxicity, an increase in resorptions and an increased incidence of visceral and skeletal variations in the offspring at the highest dose. The higher no-effect dose for rat embryofetal developmental toxicity was associated with a plasma modafinil exposure approximately 0.5 times the AUC in humans at the recommended daily dose (RHD) of 200 mg. However, in a subsequent study of up to 480 mg/kg/day (plasma modafinil exposure approximately 2 times the AUC in humans at the RHD) no adverse effects on embryofetal development were observed.

Modafinil administered orally to pregnant rabbits throughout the period of organogenesis at doses of 45, 90, and 180 mg/kg/day increased the incidences of fetal structural alterations and embryofetal death at the highest dose. The highest no-effect dose for developmental toxicity was associated with a plasma modafinil AUC approximately equal to the AUC in humans at the RHD.

Oral administration of armodafinil (the R-enantiomer of modafinil; 60, 200, or 600 mg/kg/day) to pregnant rats throughout the period of organogenesis resulted in increased incidences of fetal visceral and skeletal variations at the intermediate dose or greater and decreased fetal body weights at the highest dose. The no-effect dose for rat embryofetal developmental toxicity was associated with a plasma armodafinil exposure (AUC) approximately one-tenth times the AUC for armodafinil in humans treated with modafinil at the RHD.

Modafinil administration to rats throughout gestation and lactation at oral doses of up to 200 mg/kg/day resulted in decreased viability in the offspring at doses greater than 20 mg/kg/day (plasma modafinil AUC approximately 0.1 times the AUC in humans at the RHD). No effects on postnatal developmental and neurobehavioral parameters were observed in surviving offspring.

There are no adequate and well-controlled studies in pregnant women. Two cases of intrauterine growth retardation and one case of spontaneous abortion have been reported in association with armodafinil and modafinil. Although the pharmacology of modafinil and armodafinil is not identical to that of the sympathomimetic amines, they do share some pharmacologic properties with this class. Certain of these drugs have been associated with intrauterine growth retardation and spontaneous abortions. Whether the cases reported are drug-related is unknown.

Modafinil should be used during pregnancy only if the potential benefit justifies the potential risk to the fetus.

Labor and Delivery

The effect of modafinil on labor and delivery in humans has not been systematically investigated.

Nursing Mothers

It is not known whether modafinil or its metabolites are excreted in human milk. Because many drugs are excreted in human milk, caution should be exercised when PROVIGIL tablets are administered to a nursing woman.

Pediatric Use

Safety and effectiveness in pediatric patients, below age 16, have not been established. Serious skin rashes, including erythema multiforme major (EMM) and Stevens-Johnson Syndrome (SJS) have been associated with modafinil use in pediatric patients (see WARNINGS, Serious Rash, including Stevens-Johnson Syndrome).

In a controlled 6-week study, 165 pediatric patients (aged 5-17 years) with narcolepsy were treated with modafinil (n=123), or placebo (n=42). There were no statistically significant differences favoring modafinil over placebo in prolonging sleep latency as measured by MSLT, or in perceptions of sleepiness as determined by the clinical global impression-clinician scale (CGI-C).

In the controlled and open-label clinical studies, treatment emergent adverse events of the psychiatric and nervous system included Tourette's syndrome, insomnia, hostility, increased cataplexy, increased hypnagogic hallucinations and suicidal ideation. Transient leukopenia, which resolved without medical intervention, was also observed. In the controlled clinical study, 3 of 38 girls, ages 12 or older, treated with modafinil experienced dysmenorrhea compared to 0 of 10 girls who received placebo.

Geriatric Use

Safety and effectiveness in individuals above 65 years of age have not been established. Experience in a limited number of patients who were greater than 65 years of age in clinical trials showed an incidence of adverse experiences similar to other age groups.

ADVERSE REACTIONS

Modafinil has been evaluated for safety in over 3500 patients, of whom more than 2000 patients with excessive sleepiness associated with primary disorders of sleep and wakefulness were given at least one dose of modafinil. In clinical trials, modafinil has been found to be generally well tolerated and most adverse experiences were mild to moderate.

The most commonly observed adverse events (≥5%) associated with the use of PROVIGIL more frequently than placebo-treated patients in the placebo-controlled clinical studies in primary disorders of sleep and wakefulness were headache, nausea, nervousness, rhinitis, diarrhea, back pain, anxiety, insomnia, dizziness, and dyspepsia. The adverse event profile was similar across these studies.

In the placebo-controlled clinical trials, 74 of the 934 patients (8%) who received PROVIGIL discontinued due to an adverse experience compared to 3% of patients that received placebo. The most frequent reasons for discontinuation that occurred at a higher rate for PROVIGIL than placebo patients were headache (2%), nausea, anxiety, dizziness, insomnia, chest pain and nervousness (each <1%). In a Canadian clinical trial, a 35 year old obese narcoleptic male with a prior history of syncopal episodes experienced a 9-second episode of asystole after 27 days of modafinil treatment (300 mg/day in divided doses).

Incidence in Controlled Trials

The following table (Table 3) presents the adverse experiences that occurred at a rate of 1% or more and were more frequent in adult patients treated with PROVIGIL than in placebo-treated patients in the principal, placebo-controlled clinical trials.

The prescriber should be aware that the figures provided below cannot be used to predict the frequency of adverse experiences in the course of usual medical practice, where patient characteristics and other factors may differ from those occurring during clinical studies. Similarly, the cited frequencies cannot be directly compared with figures obtained from other clinical investigations involving different treatments, uses, or investigators. Review of these frequencies, however, provides prescribers with a basis to estimate the relative contribution of drug and non-drug factors to the incidence of adverse events in the population studied.

Table 3. Incidence Of Treatment-Emergent Adverse Experiences In Parallel-Group, Placebo-Controlled Clinical Trials^1 With PROVIGIL In Adults With Narcolepsy, OSAHS, and SWSD (200mg, 300mg and 400mg)*
Body System | Preferred Term | Modafinil (n = 934) | Placebo (n = 567)
Body as a Whole | Headache | 34% | 23%
 | Back Pain | 6% | 5%
 | Flu Syndrome | 4% | 3%
 | Chest Pain | 3% | 1%
 | Chills | 1% | 0%
 | Neck Rigidity | 1% | 0%
Cardiovascular | Hypertension | 3% | 1%
 | Tachycardia | 2% | 1%
 | Palpitation | 2% | 1%
 | Vasodilatation | 2% | 0%
Digestive | Nausea | 11% | 3%
 | Diarrhea | 6% | 5%
 | Dyspepsia | 5% | 4%
 | Dry Mouth | 4% | 2%
 | Anorexia | 4% | 1%
 | Constipation | 2% | 1%
 | Abnormal Liver Function^2 | 2% | 1%
 | Flatulence | 1% | 0%
 | Mouth Ulceration | 1% | 0%
 | Thirst | 1% | 0%
Hemic/Lymphatic | Eosinophilia | 1% | 0%
Metabolic/Nutritional | Edema | 1% | 0%
Nervous | Nervousness | 7% | 3%
 | Insomnia | 5% | 1%
 | Anxiety | 5% | 1%
 | Dizziness | 5% | 4%
 | Depression | 2% | 1%
 | Paresthesia | 2% | 0%
 | Somnolence | 2% | 1%
 | Hypertonia | 1% | 0%
 | Dyskinesia^3 | 1% | 0%
 | Hyperkinesia | 1% | 0%
 | Agitation | 1% | 0%
 | Confusion | 1% | 0%
 | Tremor | 1% | 0%
 | Emotional Lability | 1% | 0%
 | Vertigo | 1% | 0%
Respiratory | Rhinitis | 7% | 6%
 | Pharyngitis | 4% | 2%
 | Lung Disorder | 2% | 1%
 | Epistaxis | 1% | 0%
 | Asthma | 1% | 0%
Skin/Appendages | Sweating | 1% | 0%
 | Herpes Simplex | 1% | 0%
Special Senses | Amblyopia | 1% | 0%
 | Abnormal Vision | 1% | 0%
 | Taste Perversion | 1% | 0%
 | Eye Pain | 1% | 0%
Urogenital | Urine Abnormality | 1% | 0%
 | Hematuria | 1% | 0%
 | Pyuria | 1% | 0%
* Six double-blind, placebo-controlled clinical studies in narcolepsy, OSAHS, and SWSD.
^1 Events reported by at least 1% of patients treated with PROVIGIL that were more frequent than in the placebo group are included; incidence is rounded to the nearest 1%. The adverse experience terminology is coded using a standard modified COSTART Dictionary.
Events for which the PROVIGIL incidence was at least 1%, but equal to or less than placebo are not listed in the table. These events included the following: infection, pain, accidental injury, abdominal pain, hypothermia, allergic reaction, asthenia, fever, viral infection, neck pain, migraine, abnormal electrocardiogram, hypotension, tooth disorder, vomiting, periodontal abscess, increased appetite, ecchymosis, hyperglycemia, peripheral edema, weight loss, weight gain, myalgia, leg cramps, arthritis, cataplexy, thinking abnormality, sleep disorder, increased cough, sinusitis, dyspnea, bronchitis, rash, conjunctivitis, ear pain, dysmenorrhea^4, urinary tract infection.
^2 Elevated liver enzymes.
^3 Oro-facial dyskinesias.
^4 Incidence adjusted for gender.

Dose Dependency of Adverse Events

In the adult placebo-controlled clinical trials which compared doses of 200, 300, and 400 mg/day of PROVIGIL and placebo, the only adverse events that were clearly dose related were headache and anxiety.

Vital Sign Changes

While there was no consistent change in mean values of heart rate or systolic and diastolic blood pressure, the requirement for antihypertensive medication was slightly greater in patients on PROVIGIL compared to placebo (See PRECAUTIONS).

Weight Changes

There were no clinically significant differences in body weight change in patients treated with PROVIGIL compared to placebo-treated patients in the placebo-controlled clinical trials.

Laboratory Changes

Clinical chemistry, hematology, and urinalysis parameters were monitored in Phase 1, 2, and 3 studies. In these studies, mean plasma levels of gamma glutamyltransferase (GGT) and alkaline phosphatase (AP) were found to be higher following administration of PROVIGIL, but not placebo. Few subjects, however, had GGT or AP elevations outside of the normal range. Shifts to higher, but not clinically significantly abnormal, GGT and AP values appeared to increase with time in the population treated with PROVIGIL in the Phase 3 clinical trials. No differences were apparent in alanine aminotransferase, aspartate aminotransferase, total protein, albumin, or total bilirubin.

ECG Changes

No treatment-emergent pattern of ECG abnormalities was found in placebo-controlled clinical trials following administration of PROVIGIL.

Postmarketing Reports

The following adverse reactions have been identified during post-approval use of PROVIGIL. Because these reactions are reported voluntarily from a population of uncertain size, it is not possible to reliably estimate their frequency or establish a causal relationship to drug exposure. Decisions to include these reactions in labeling are typically based on one or more of the following factors: (1) seriousness of the reaction, (2) frequency of the reporting, or (3) strength of causal connection to PROVIGIL.

Hematologic: agranulocytosis

DRUG ABUSE AND DEPENDENCE

Controlled Substance Class

Modafinil (PROVIGIL) is listed in Schedule IV of the Controlled Substances Act.

Abuse Potential and Dependence

In addition to its wakefulness-promoting effect and increased locomotor activity in animals, in humans, PROVIGIL produces psychoactive and euphoric effects, alterations in mood, perception, thinking and feelings typical of other CNS stimulants. In in vitro binding studies, modafinil binds to the dopamine reuptake site and causes an increase in extracellular dopamine, but no increase in dopamine release. Modafinil is reinforcing, as evidenced by its self-administration in monkeys previously trained to self-administer cocaine. In some studies, modafinil was also partially discriminated as stimulant-like. Physicians should follow patients closely, especially those with a history of drug and/or stimulant (e.g., methylphenidate, amphetamine, or cocaine) abuse. Patients should be observed for signs of misuse or abuse (e.g., incrementation of doses or drug-seeking behavior).

The abuse potential of modafinil (200, 400, and 800 mg) was assessed relative to methylphenidate (45 and 90 mg) in an inpatient study in individuals experienced with drugs of abuse. Results from this clinical study demonstrated that modafinil produced psychoactive and euphoric effects and feelings consistent with other scheduled CNS stimulants (methylphenidate).

Withdrawal

The effects of modafinil withdrawal were monitored following 9 weeks of modafinil use in one US Phase 3 controlled clinical trial. No specific symptoms of withdrawal were observed during 14 days of observation, although sleepiness returned in narcoleptic patients.

OVERDOSAGE

Human Experience

In clinical trials, a total of 151 protocol-specified doses ranging from 1000 to 1600 mg/day (5 to 8 times the recommended daily dose of 200 mg) have been administered to 32 subjects, including 13 subjects who received doses of 1000 or 1200 mg/day for 7 to 21 consecutive days. In addition, several intentional acute overdoses occurred; the two largest being 4500 mg and 4000 mg taken by two subjects participating in foreign depression studies. None of these study subjects experienced any unexpected or life-threatening effects. Adverse experiences that were reported at these doses included excitation or agitation, insomnia, and slight or moderate elevations in hemodynamic parameters. Other observed high-dose effects in clinical studies have included anxiety, irritability, aggressiveness, confusion, nervousness, tremor, palpitations, sleep disturbances, nausea, diarrhea and decreased prothrombin time.

From post-marketing experience, there have been no reports of fatal overdoses involving modafinil alone (doses up to 12 grams). Overdoses involving multiple drugs, including modafinil, have resulted in fatal outcomes. Symptoms most often accompanying modafinil overdose, alone or in combination with other drugs have included: insomnia; central nervous system symptoms such as restlessness, disorientation, confusion, excitation and hallucination; digestive changes such as nausea and diarrhea; and cardiovascular changes such as tachycardia, bradycardia, hypertension and chest pain.

Cases of accidental ingestion/overdose have been reported in children as young as 11 months of age. The highest reported accidental ingestion on a mg/kg basis occurred in a three-year-old boy who ingested 800-1000 mg (50-63 mg/kg) of modafinil. The child remained stable. The symptoms associated with overdose in children were similar to those observed in adults.

Overdose Management

No specific antidote to the toxic effects of modafinil overdose has been identified to date. Such overdoses should be managed with primarily supportive care, including cardiovascular monitoring. If there are no contraindications, induced emesis or gastric lavage should be considered. There are no data to suggest the utility of dialysis or urinary acidification or alkalinization in enhancing drug elimination. The physician should consider contacting a poison-control center on the treatment of any overdose.

DOSAGE AND ADMINISTRATION

The recommended dose of PROVIGIL is 200 mg given once a day.

For patients with narcolepsy and OSAHS, PROVIGIL should be taken as a single dose in the morning.

For patients with SWSD, PROVIGIL should be taken approximately 1 hour prior to the start of their work shift.

Doses up to 400 mg/day, given as a single dose, have been well tolerated, but there is no consistent evidence that this dose confers additional benefit beyond that of the 200 mg dose (See CLINICAL PHARMACOLOGY and CLINICAL TRIALS).

General Considerations

Dosage adjustment should be considered for concomitant medications that are substrates for CYP3A4, such as triazolam and cyclosporine (See PRECAUTIONS, Drug Interactions).

Drugs that are largely eliminated via CYP2C19 metabolism, such as diazepam, propranolol, phenytoin (also via CYP2C9) or S-mephenytoin may have prolonged elimination upon coadministration with PROVIGIL and may require dosage reduction and monitoring for toxicity.

In patients with severe hepatic impairment, the dose of PROVIGIL should be reduced to one-half of that recommended for patients with normal hepatic function (See CLINICAL PHARMACOLOGY and PRECAUTIONS).

There is inadequate information to determine safety and efficacy of dosing in patients with severe renal impairment (See CLINICAL PHARMACOLOGY and PRECAUTIONS).

In elderly patients, elimination of PROVIGIL and its metabolites may be reduced as a consequence of aging. Therefore, consideration should be given to the use of lower doses in this population (SeeCLINICAL PHARMACOLOGY and PRECAUTIONS).

HOW SUPPLIED:

PROVIGIL® (modafinil) Tablets

100 mg: Each capsule-shaped, white, uncoated tablet is debossed with "PROVIGIL" on one side and "100 MG" on the other.

NDC 21695-234-15 - Bottles of 15

NDC 21695-234-30 - Bottles of 30

200 mg: Each capsule-shaped, white, scored, uncoated tablet is debossed with "PROVIGIL" on one side and "200 MG" on the other.

NDC 21695-235-15 - Bottles of 15

NDC 21695-235-30 - Bottles of 30

Store at 20° - 25° C (68° - 77° F).

Manufactured for:

Cephalon, Inc.

Frazer, PA 19355

U.S. Patent Nos. RE37,516 / 4,927,855

© Cephalon, Inc., 2008. All rights reserved

March 2008

PROV-011

Repackaged by:

Rebel Distributors Corp

Thousand Oaks, CA 91320

Repackaging and Relabeling by:
Physicians Total Care, Inc.
Tulsa, OK 74146

Patient Information

PROVIGIL® (pro-vij-el) Tablets [C-IV]

Generic name: modafinil

Read the Patient Information that comes with PROVIGIL before you start taking it and each time you get a refill. There may be new information. This leaflet does not take the place of talking with your doctor about your condition or treatment.

What is the most important information I should know about PROVIGIL?

1. PROVIGIL may cause you to have a serious rash or a serious allergic reaction. Stop PROVIGIL and call your doctor right away or get emergency treatment if you have any of the following:

- skin rash, hives, sores in your mouth, or your skin blisters and peels
- swelling of your face, eyes, lips, tongue, or throat
- trouble swallowing or breathing
- hoarse voice

2. PROVIGIL is not approved for use in children.

What is PROVIGIL?

PROVIGIL is a prescription medicine used to improve awakeness in adults who are very sleepy due to one of the following diagnosed sleep problems:

- shift work sleep disorder (SWSD)
- obstructive sleep apnea/hypopnea syndrome (OSAHS). PROVIGIL is used along with other medical treatments for this sleep problem. PROVIGIL is not a replacement for your CPAP machine. It is important that you continue to use your CPAP machine while sleeping.
- narcolepsy

You should be diagnosed with one of these sleep disorders before taking PROVIGIL. Sleepiness can be a symptom of other medical conditions that need to be treated.

- PROVIGIL will not cure the above sleep disorders. PROVIGIL may help the sleepiness caused by these conditions, but it may not stop all your sleepiness.
- PROVIGIL does not take the place of getting enough sleep.
- Follow your doctor's advice about good sleep habits and using other treatments.

Box Warning

PROVIGIL is a federally controlled substance (C-IV) because it can be abused or lead to dependence. Keep PROVIGIL in a safe place to prevent misuse and abuse. Selling or giving away PROVIGIL may harm others, and is against the law. Tell your doctor if you have ever abused or been dependent on alcohol, prescription medicines or street drugs.

Patient Information

Who should not take PROVIGIL?

Do not take PROVIGIL if you:

- are allergic to any of its ingredients.The active ingredient is modafinil. See the end of this leaflet for a complete list of ingredients.
- have had a rash or allergic reaction to armodafinil, the active ingredient in NUVIGIL™, because these medicines are very similar.

PROVIGIL is not approved for use in children.

What should I tell my doctor before starting PROVIGIL?

Tell your doctor about all of your health conditions including, if you:

- have a history of mental health problems
- have heart problems or had a heart attack
- have high blood pressure
- have liver or kidney problems
- have a history of drug or alcohol abuse or addiction
- have ever had a mental problem called psychosis.
- are pregnant or planning to become pregnant. It is not known if PROVIGIL may harm your unborn baby.
- are breastfeeding. It is not known if PROVIGIL passes into your milk or if it can harm your baby.

Tell your doctor about all the medicines you take, including prescription and non-prescription medicines, vitamins, and herbal supplements. PROVIGIL and many other medicines can interact with each other, sometimes causing side effects. PROVIGIL may affect the way other medicines work, and other medicines may affect how PROVIGIL works. Especially, tell your doctor if you use a hormonal birth control method. PROVIGIL can affect hormonal birth control methods. Hormonal birth control methods include pills, shots, implants, patches, vaginal rings, and intrauterine devices (IUDs). Women who use hormonal birth control with PROVIGIL may have a higher chance for getting pregnant while taking PROVIGIL, and for one month after stopping PROVIGIL. Talk to your doctor about birth control methods that are right for you while using PROVIGIL.

Keep a list of all the medicines you take. Your doctor or pharmacist will tell you if it is safe to take PROVIGIL and other medicines together. Do not take other medicines with PROVIGIL unless your doctor has told you it is okay.

How should I take PROVIGIL?

- Take PROVIGIL exactly as prescribed by your doctor. Your doctor will prescribe the dose of PROVIGIL that is right for you. Do not change your dose of PROVIGIL without talking to your doctor. Do not take more PROVIGIL than prescribed.
- Your doctor will tell you the right time of day to take PROVIGIL.
- If you take more than your prescribed dose or overdose, call your doctor or poison control center right away.

What should I avoid while taking PROVIGIL?

- Do not drive a car or do other dangerous activities until you know how PROVIGIL affects you. People with sleep disorders should always be careful about doing things that could be dangerous. Do not change your daily habits until your doctor tells you it is okay.
- Avoid drinking alcohol.

What are the possible side effects of PROVIGIL?

PROVIGIL may cause serious side effects. Call your doctor or get emergency help if you get any of the following:

- a serious rash or serious allergic reaction. (See, "What is the most important information I should know about PROVIGIL".)
- mental (psychiatric) symptoms. Symptoms include depression, anxiety, hallucinations, mania, thoughts of suicide, aggression, or other mental problems.
- heart problems including chest pain

The most common side effects of PROVIGIL are headache, nausea, nervousness, stuffy nose, diarrhea, back pain, anxiety, trouble sleeping, dizziness, and upset stomach.

PROVIGIL may cause allergic reactions. If you get a rash, hives or other allergic reaction, stop taking PROVIGIL and call your doctor right away.

If you have either of the problems listed below or any other serious side effects while taking PROVIGIL stop taking PROVIGIL and call your doctor or get emergency help:

- chest pain.
- mental problems.

Some effects of PROVIGIL on the brain are the same as other medicines called "stimulants". These effects may lead to abuse or dependence on PROVIGIL. Before starting PROVIGIL, tell your doctor if you have ever abused drugs, including other stimulant medicines.

Tell your doctor if you get any side effect that bothers you or that does not go away while taking PROVIGIL.

These are not all the side effects of PROVIGIL. For more information, ask your doctor or pharmacist.

How should I store PROVIGIL?

- Store PROVIGIL at room temperature, 68° to 77° F (20° to 25° C).
- Keep PROVIGIL and all medicines out of the reach of children.

General information about PROVIGIL

Medicines are sometimes prescribed for conditions that are not listed in patient information leaflets. Do not use PROVIGIL for a condition for which it was not prescribed. Do not give PROVIGIL to other people, even if they have the same symptoms you have. It may harm them and it is against the law.

This leaflet summarizes the most important information about PROVIGIL. If you would like more information, talk with your doctor. You can ask your doctor or pharmacist for information about PROVIGIL that is written for health professionals. For more information, please call 1-800-896-5855, or go to www.PROVIGIL.com.

What are the ingredients in PROVIGIL?

Active Ingredient: modafinil

Inactive Ingredients: croscarmellose sodium, lactose, magnesium stearate, microcrystalline cellulose, povidone, and pregelatinized starch.

Rx Only

PROVIGIL® (modafinil) Tablets